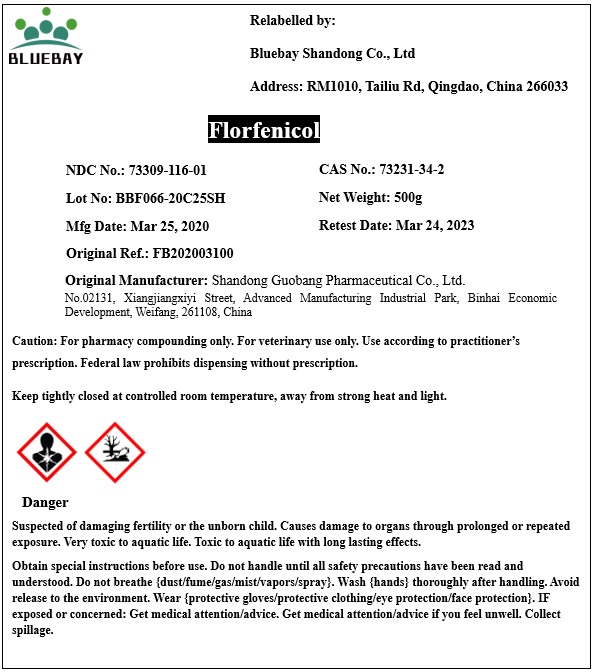 DRUG LABEL: Florfenicol
NDC: 73309-116 | Form: POWDER
Manufacturer: BLUEBAY SHANDONG CO.,LTD
Category: other | Type: BULK INGREDIENT
Date: 20200413

ACTIVE INGREDIENTS: Florfenicol 1 g/1 g

Florfenicol